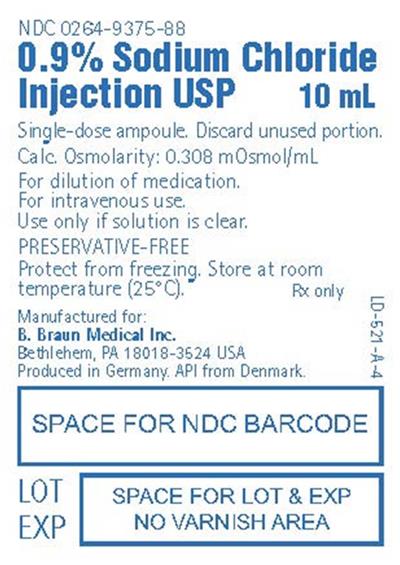 DRUG LABEL: Sodium Chloride
NDC: 0264-9375 | Form: INJECTION
Manufacturer: B. Braun Medical Inc.
Category: prescription | Type: HUMAN PRESCRIPTION DRUG LABEL
Date: 20220314

ACTIVE INGREDIENTS: SODIUM CHLORIDE 9 mg/1 mL

0.9% Sodium Chloride Injection USP

DESCRIPTION

Each 1 mL of 0.9% Sodium Chloride Injection USP contains:

Sodium Chloride USP 9 mg
Water for Injection USP qs

pH: 5.6 (4.5-7.0)

Calculated Osmolarity: 0.308 mOsmol/mL

pH adjusted with Hydrochloric Acid NF

Concentration of Electrolytes (mEq/liter): Sodium 154 Chloride 154

0.9% Sodium Chloride Injection USP is sterile, nonpyrogenic, isotonic and contains no bacteriostatic or antimicrobial agents.

The formula of the active ingredient is:

Ingredient | Molecular Formula | Molecular Weight
Sodium Chloride USP | NaCI | 58.44

Not made with natural rubber latex, PVC or DEHP.

CLINICAL PHARMACOLOGY

0.9% Sodium Chloride Injection USP provides electrolytes and is a source of water for hydration. It is capable of inducing diuresis depending on the clinical condition of the patient.

Sodium, the major cation of the extracellular fluid, functions primarily in the control of water distribution, fluid balance, and osmotic pressure of body fluids. Sodium is also associated with chloride and bicarbonate in the regulation of the acid-base equilibrium of body fluid.

Chloride, the major extracellular anion, closely follows the metabolism of sodium, and changes in the acid-base balance of the body are reflected by changes in the chloride concentration.

INDICATIONS AND USAGE

0.9% Sodium Chloride Injection USP is indicated as pharmaceutic aid and diluent for the infusion of compatible drug additives. Refer to prescribing information accompanying additive drugs.

CONTRAINDICATIONS

This solution is contraindicated where the administration of sodium or chloride could be clinically detrimental.

WARNINGS

The administration of intravenous solutions can cause fluid and/or solute overload resulting in dilution of serum electrolyte concentrations, overhydration, congested states or pulmonary edema. The risk of dilutional states is inversely proportional to the electrolyte concentration. The risk of solute overload causing congested states with peripheral and pulmonary edema is directly proportional to the electrolyte concentration.

Solutions containing sodium ions should be used with great care, if at all, in patients with congestive heart failure, severe renal insufficiency, and in clinical states in which there is sodium retention with edema. In patients with diminished renal function, administration of solutions containing sodium ions may result in sodium retention.

Infusion of isotonic (0.9%) sodium chloride during or immediately after surgery may result in excessive sodium retention. Use the patient’s circulatory system status as a guide.

PRECAUTIONS

General

Clinical evaluation and periodic laboratory determinations are necessary to monitor changes in fluid balance, electrolyte concentrations, and acid-base balance during prolonged parenteral therapy or whenever the condition of the patient warrants such evaluation. Significant deviations from normal concentrations may require tailoring of the electrolyte pattern, in these or alternative solutions.

Since Sodium Chloride Injection does not contain antimicrobial agents and is intended for single use, any unused amount must be discarded immediately following withdrawal of any portion of the contents of the ampoule. Do not open ampoule until it is to be used.

This solution should be used with care in patients with hypervolemia, renal insufficiency, urinary tract obstruction, or impending or frank cardiac decompensation.

Consult the manufactures instructions for choice of vehicle, appropriate dilution or volume for dissolving the drug to be injected, including the route and rate of injection.

Extraordinary electrolyte losses such as may occur during protracted nasogastric suction, vomiting, diarrhea or gastrointestinal fistula drainage may necessitate additional electrolyte supplementation.

Additional essential electrolytes, minerals and vitamins should be supplied as needed.

Sodium-containing solutions should be administered with caution to patients receiving corticosteroids or corticotropin, or to other salt-retaining patients. Care should be exercised in administering solutions containing sodium to patients with renal or cardiovascular insufficiency, with or without congestive heart failure, particularly if they are postoperative or elderly.

Infusion of more than one liter of isotonic (0.9%) sodium chloride per day may supply more sodium and chloride than normally found in serum, and can exceed normal tolerance, resulting in hypernatremia; this may also cause a loss of bicarbonate ions, resulting in an acidifying effect.

To minimize the risk of possible incompatibilities arising from mixing this solution with other additives that may be prescribed, the final infusate should be inspected for cloudiness or precipitation immediately after mixing, prior to administration and periodically during administration.

If administration is controlled by a pumping device, care must be taken to discontinue pumping action before the container runs dry or air embolism may result.

This solution is intended for intravenous administration using sterile equipment. It is recommended that intravenous administration apparatus be replaced at least once every 24 hours.

Use only if solution is clear and container and glass ampoule is intact.

Carcinogenesis, Mutagenesis, Impairment of Fertility

Studies with 0.9% Sodium Chloride Injection USP have not been performed to evaluate carcinogenic potential, mutagenic potential or effects on fertility.

Pregnancy

Teratogenic Effects

Pregnancy Category C. Animal reproduction studies have not been conducted with 0.9% Sodium Chloride Injection USP. It is also not known whether 0.9% Sodium Chloride Injection USP can cause fetal harm when administered to a pregnant woman or can affect reproduction capacity. 0.9% Sodium Chloride Injection USP should be given to a pregnant woman only if clearly needed.

Nursing Mothers

It is not known whether this drug is excreted in human milk. Because many drugs are excreted in human milk, caution should be exercised when 0.9% Sodium Chloride Injection USP is administered to a nursing woman.

Pediatric Use

Safety and effectiveness of sodium chloride injections in pediatric patients have not been established by adequate and well controlled trials, however, the use of electrolyte solutions in the pediatric population is referenced in the medical literature. The warnings, precautions and adverse reactions identified in the label copy should be observed in the pediatric population.

Geriatric Use

An evaluation of current literature revealed no clinical experience identifying differences in response between elderly and younger patients. In general, dose selection for an elderly patient should be cautious, usually starting at the low end of the dosing range, reflecting the greater frequency of decreased hepatic, renal, or cardiac function, and of concomitant disease or other drug therapy.

This drug is known to be substantially excreted by the kidney, and the risk of toxic reactions may be greater in patients with impaired renal function. Because elderly patients are more likely to have decreased renal function, care should be taken in dose selection, and it may be useful to monitor renal function.

ADVERSE REACTIONS

Reactions which may occur because of the solution, added drugs or the technique of reconstitution or administration include febrile response, infection at the site of injection, venous thrombosis or phlebitis extending from the site of injection, extravasation and hypervolemia. Carefully review the prescribing information for the diluted drug.

The physician should also be alert to the possibility of adverse reactions to drug additives. Prescribing information for drug additives to be administered in this manner should be consulted.

Symptoms may result from an excess or deficit of one or more of the ions present in the solution; therefore, frequent monitoring of electrolyte levels is essential.

Hypernatremia may be associated with edema and exacerbation of congestive heart failure due to the retention of water, resulting in an expanded extracellular fluid volume.

If infused in large amounts, chloride ions may cause a loss of bicarbonate ions, resulting in an acidifying effect.

If an adverse reaction does occur, discontinue the infusion, evaluate the patient, institute appropriate therapeutic countermeasures, and save the remainder of the fluid for examination if deemed necessary.

OVERDOSAGE

In the event of a fluid or solute overload during parenteral therapy, reevaluate the patient’s condition and institute appropriate corrective treatment.

DOSAGE AND ADMINISTRATION

This solution is for intravenous use only.

Dosage is to be directed by a physician and is dependent upon age, weight, clinical condition of the patient and laboratory determinations. Frequent laboratory determinations and clinical evaluation are essential to monitor changes in blood glucose and electrolyte concentrations, and fluid and electrolyte balance during prolonged parenteral therapy.

In the average adult, daily requirements of sodium and chloride are met by the infusion of one liter of 0.9% sodium chloride (154 mEq each of sodium and chloride).

There is no specific pediatric dose. The dose is dependent on weight, clinical condition and laboratory results. Follow recommendations of appropriate pediatric reference text. (See PRECAUTIONS, Pediatric Use.)

Fluid administration should be based on calculated maintenance or replacement fluid requirements for each patient.

0.9% Sodium Chloride Injection USP may also be administered intravascularly as a priming fluid in hemodialysis procedures.

When Sodium Chloride Injections USP are used as diluents for infusion of compatible drug additives, refer to dosage and administration information accompanying additive drugs.

Some additives may be incompatible. Consult with pharmacist. When introducing additives, use aseptic techniques. Mix thoroughly.

Do not store.

Parenteral drug products should be inspected visually for particulate matter and discoloration prior to administration, whenever solution and container permit.

HOW SUPPLIED

0.9% Sodium Chloride Injection USP is supplied sterile and nonpyrogenic in glass ampoule container.

NDC | Size
0264-9375-88 | 10 mL

Exposure of pharmaceutical products to heat should be minimized. Avoid excessive heat. Protect from freezing. It is recommended that the product be stored at room temperature (25°C); however, brief exposure up to 40°C does not adversely affect the product.

Revised: May 2018

Directions for Use of Ampoule

To open ampoules, using gauze, place thumb and forefinger on color line, break at constriction.

NOTE: Before use, perform the following checks:

- Inspect each container. Read the label. Ensure solution is the one ordered and is within the expiration date.
- Invert container and carefully inspect the solution in good light for cloudiness, haze, or particulate matter. Any container which is suspect should not be used.
- Use only if solution is clear and container and seals are intact.

A4800327-2

Package Insert

Rx only

Manufactured for:

B. Braun Medical Inc.

Bethlehem, PA 18018-3524 USA

Produced in Germany. API from Denmark.

Manufactured by:

Solupharm Pharmazeutische Erzeugnisse GmbH

PRINCIPAL DISPLAY PANEL

NDC 0264-9375-88

0.9% Sodium Chloride Injection USP

10 mL

Single-dose ampoule. Discard unused portion.

Calc. Osmolarity: 0.308 mOsmol/mL

For dilution of medication.

For intravenous use.

Use only if solution is clear.

PRESERVATIVE-FREE

Protect from freezing. Store at room

temperature (25°C).

Rx only

Manufactured for:

B. Braun Medical Inc.

Bethlehem, PA 18018-3524 USA

Produced in Germany, API from Denmark.

LD-521-A-4

LOT
EXP